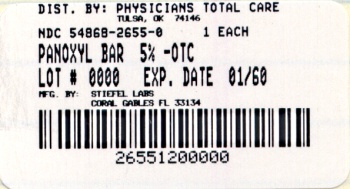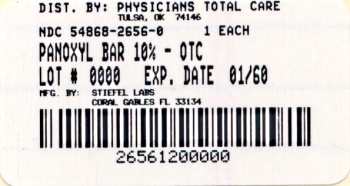 DRUG LABEL: PanOxyl
NDC: 54868-2656 | Form: SOAP
Manufacturer: Physicians Total Care, Inc.
Category: otc | Type: HUMAN OTC DRUG LABEL
Date: 20110520

ACTIVE INGREDIENTS: BENZOYL PEROXIDE 11.3 g/1 1
INACTIVE INGREDIENTS: CETOSTEARYL ALCOHOL; COCAMIDOPROPYL BETAINE; GLYCERIN; HYDROGENATED CASTOR OIL; LACTIC ACID; MINERAL OIL; POTASSIUM PHOSPHATE; WATER; SILICON DIOXIDE; SODIUM LAURYL SULFATE; TITANIUM DIOXIDE; STARCH, CORN

Drug Facts

Active ingredient (Maximum Strength)

Benzoyl peroxide 10%

Active ingredient (Regular Strength)

Benzoyl peroxide 5%

Purpose

Acne medication

INDICATIONS AND USAGE

Use for the treatment of acne; helps prevent new acne blemishes from forming

Warnings

For external use only

Do not use

- if you have very sensitive skin
- if you are sensitive to benzoyl peroxide

When using this product

- skin irritation and dryness is more likely to occur if you use another topical acne medication at the same time. If irritation occurs, only use one topical acne medication at a time
- avoid unnecessary sun exposure and use a sunscreen
- avoid contact with the eyes, lips, and mouth
- avoid contact with hair and dyed fabrics, which may be bleached by this product
- skin irritation may occur, characterized by redness, burning, itching, peeling, or possibly swelling. Irritation may be reduced by using the product less frequently or in a lower concentration.

Stop use and ask a doctor if

- irritation becomes severe.

Keep out of reach of children.

If swallowed, get medical help or contact a Poison Control Center right away.

Directions

- using warm water, wash the affected area for 1 to 2 minutes
- rinse well and pat dry with a clean towel
- because too much drying of the skin may occur, start with 1 application daily, then gradually increase to 2 or 3 times daily if needed or as directed by a doctor
- if bothersome dryness or peeling occurs, reduce application to once a day or every other day
- If going outside, apply sunscreen after using this product. If irritation or sensitivity develops, stop use of both products and ask a doctor.

Other information

Store at controlled room temperature 59° -86°F (15°-30°C).

Inactive ingredients

cetearyl alcohol, cocamidopropyl betaine, glycerin, hydrogenated castor oil, lactic acid, mineral oil, PEG-14M, potassium lauryl sulfate, potassium phosphate, purified water, silica, sodium lauryl sulfate, titanium dioxide, zea mays (corn) starch

Questions?

call 1-888-784-3335 (STIEFEL). Side effects associated with use of this product may be reported to this number.

Maximum Strength

Now you can take control of your acne with Maximum Strength PanOxyl® Acne Cleansing Bar, the highest strength of Benzoyl Peroxide (BPO) available without a prescription. The Benzoyl Peroxide in the PanOxyl® Acne Cleansing Bar is the same medicine prescribed by dermatologists.

The convenient bar form of PanOxyl® gently removes dirt and excess oil to cleanse and unclog pores, making it an excellent choice for the management of acne on the face, chest and back.

Regular Strength

Now you can take control of your acne with the PanOxyl® Acne Cleansing Bar. The 5% Benzoyl Peroxide in the PanOxyl® Acne Cleansing Bar is the same medicine prescribed by dermatologists.

The convenient bar form of PanOxyl® Acne Cleansing Bar gently removes dirt and excess oil to cleanse and unclog pores, making it an excellent choice for the management of acne on the face, chest and back.

PANOXYL is a registered trademark of Stiefel Laboratories, Inc.

www.stiefelchc.com

©2010 Stiefel Laboratories, Inc.

Stiefel Laboratories, Inc.

Research Triangle Park, NC 27709

Relabeling by:
Physicians Total Care, Inc.
Tulsa, OK 74146

Principal Display Panel

NDC 54868-2656-0

PanOxyl®

10% Benzoyl Peroxide

Maximum Strength

ACNE CLEANSING BAR

DERMATOLOGIST Recommended Ingredients

Therapeutic acne control

FACE

CHEST

BACK

- Benzoyl Peroxide effectively penetrates pores killing the bacteria that cause acne
- Clears existing acne blemishes and prevents new blemishes from forming

Net Wt 4 Oz (113 g)

Principal Display Panel

NDC 54868-2655-0

PanOxyl®

5% Benzoyl Peroxide

Regular Strength

ACNE CLEANSING BAR

DERMATOLOGIST Recommended Ingredients

Therapeutic acne control

FACE

CHEST

BACK

- Benzoyl Peroxide effectively penetrates pores killing the bacteria that cause acne
- Clears existing acne blemishes and prevents new blemishes from forming

Net Wt 4 Oz (113 g)